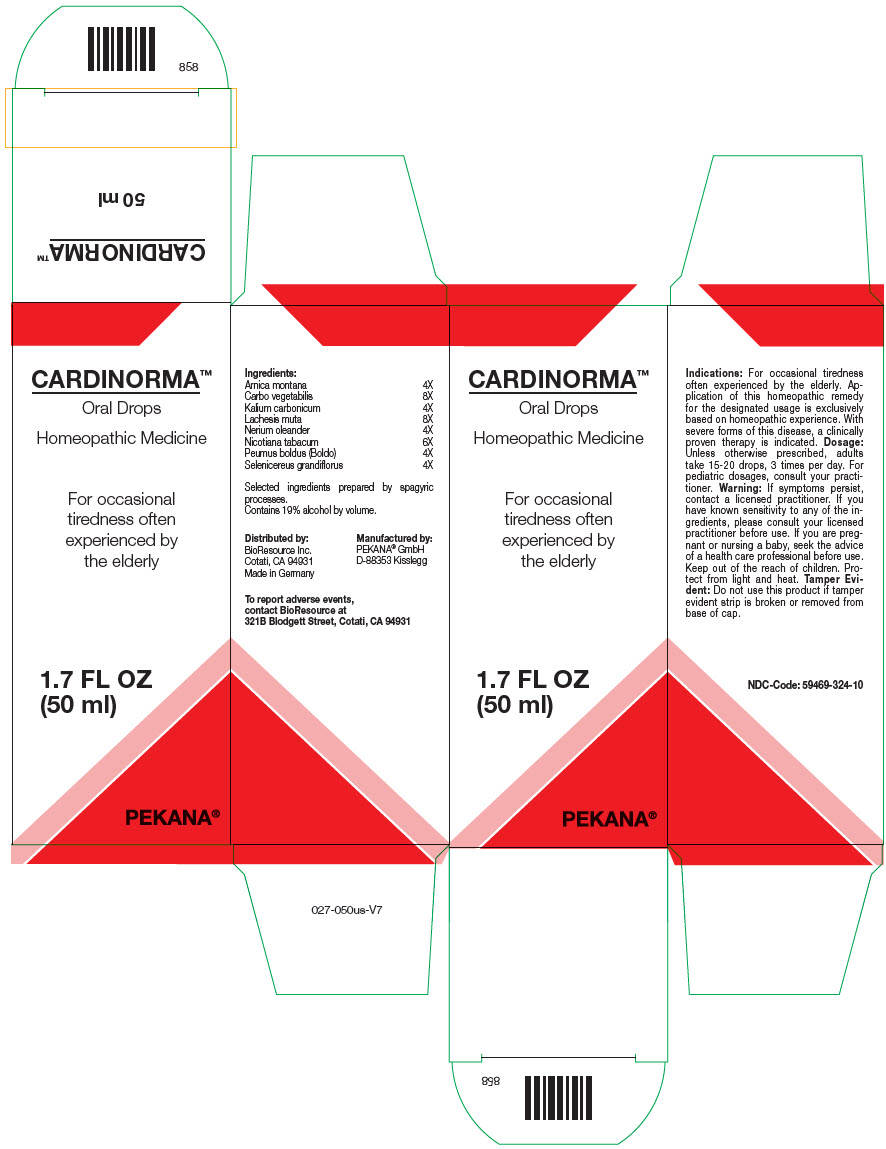 DRUG LABEL: CARDINORMA
NDC: 59469-324 | Form: SOLUTION/ DROPS
Manufacturer: PEKANA Naturheilmittel GmbH
Category: homeopathic | Type: HUMAN OTC DRUG LABEL
Date: 20230111

ACTIVE INGREDIENTS: ARNICA MONTANA ROOT 4 [hp_X]/50 mL; ACTIVATED CHARCOAL 8 [hp_X]/50 mL; POTASSIUM CARBONATE 4 [hp_X]/50 mL; LACHESIS MUTA VENOM 8 [hp_X]/50 mL; NERIUM OLEANDER LEAF 4 [hp_X]/50 mL; TOBACCO LEAF 6 [hp_X]/50 mL; PEUMUS BOLDUS LEAF 4 [hp_X]/50 mL; SELENICEREUS GRANDIFLORUS WHOLE 4 [hp_X]/50 mL
INACTIVE INGREDIENTS: WATER; ALCOHOL

CARDINORMA™

ACTIVE INGREDIENT

Ingredients:
Arnica montana | 4X
Carbo vegetabilis | 8X
Kalium carbonicum | 4X
Lachesis muta | 8X
Nerium oleander | 4X
Nicotiana tabacum | 6X
Peumus boldus (Boldo) | 4X
Selenicereus grandiflorus | 4X

Selected ingredients prepared by spagyric processes.

INACTIVE INGREDIENT

Contains 19% alcohol by volume.

Indications

PURPOSE

For occasional tiredness often experienced by the elderly. Application of this homeopathic remedy for the designated usage is exclusively based on homeopathic experience. With severe forms of this disease, a clinically proven therapy is indicated.

Dosage

Unless otherwise prescribed, adults take 15-20 drops, 3 times per day. For pediatric dosages, consult your practitioner.

Warning

If symptoms persist, contact a licensed practitioner. If you have known sensitivity to any of the ingredients, please consult your licensed practitioner before use. If you are pregnant or nursing a baby, seek the advice of a health care professional before use.

Keep out of the reach of children.

STORAGE AND HANDLING

Protect from light and heat.

Tamper Evident

Do not use this product if tamper evident strip is broken or removed from base of cap.

QUESTIONS

To report adverse events, contact BioResource at 321B Blodgett Street, Cotati, CA 94931

Distributed by:
BioResource Inc.
Cotati, CA 94931

Manufactured by:
PEKANA® GmbH
D-88353 Kisslegg

PRINCIPAL DISPLAY PANEL - 50 ml Bottle Box

CARDINORMA™
Oral Drops

Homeopathic Medicine

For occasional
tiredness often
experienced by
the elderly

1.7 FL OZ
(50 ml)

PEKANA®